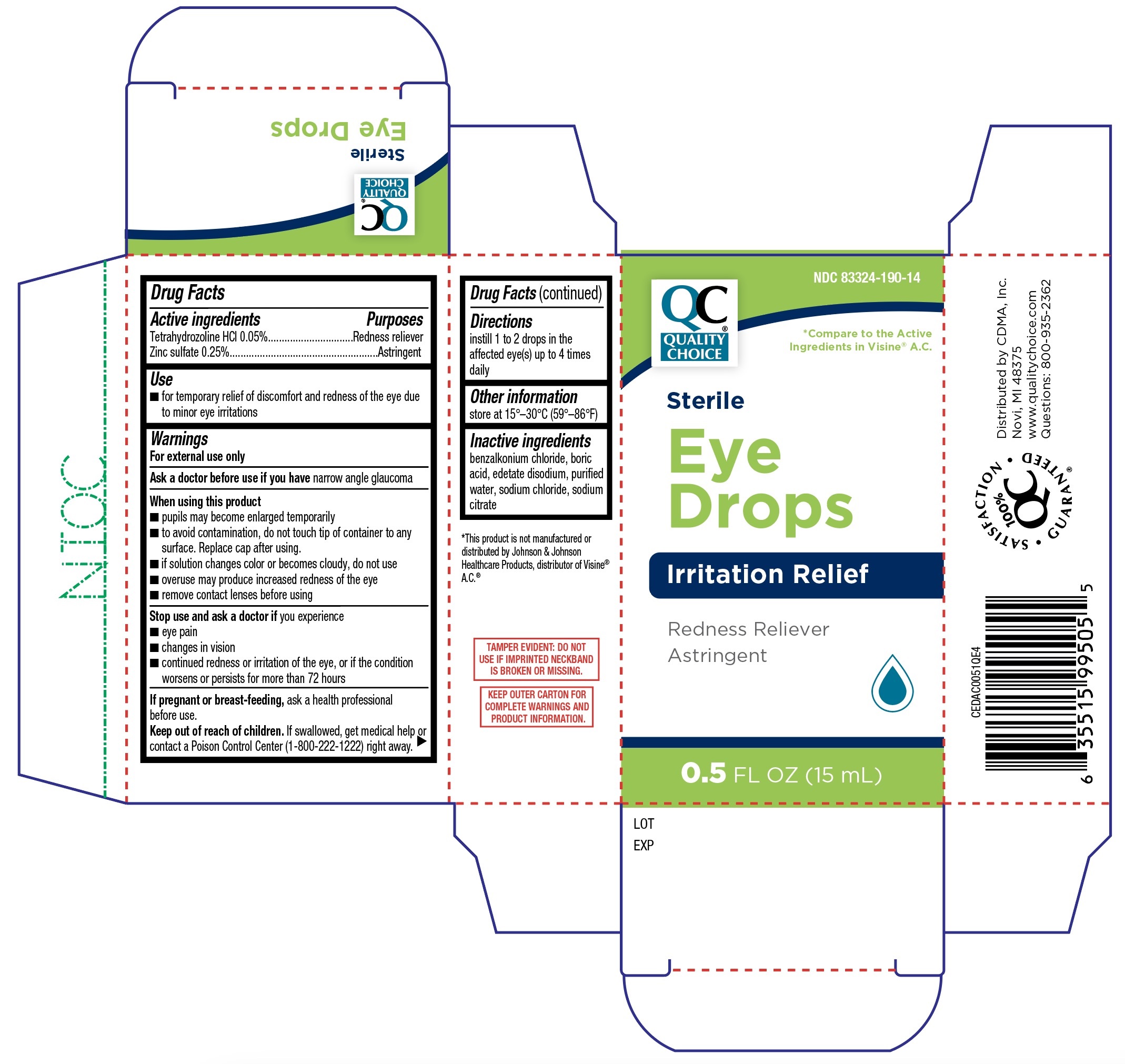 DRUG LABEL: Quality Choice Eye Drops Irritation Relief
NDC: 83324-190 | Form: SOLUTION/ DROPS
Manufacturer: Quality Choice
Category: otc | Type: HUMAN OTC DRUG LABEL
Date: 20251230

ACTIVE INGREDIENTS: TETRAHYDROZOLINE HYDROCHLORIDE 0.05 g/100 mL; ZINC SULFATE 0.25 g/100 mL
INACTIVE INGREDIENTS: WATER; BENZALKONIUM CHLORIDE; BORIC ACID; EDETATE DISODIUM; SODIUM CHLORIDE; SODIUM CITRATE

Quality Choice Eye Drops Irritation Relief (PLD)

Active ingredients

Tetrahydrozoline HCl 0.05%

Zinc sulfate 0.25%

Purposes

Redness reliever

Astringent

Use

- for temporary relief of discomfort and redness of the eye due to minor eye irritation

Warnings

For external use only

Ask a doctor before use if you have

narrow angle glaucoma

When using this product

- pupils may become enlarged temporarily
- to avoid contamination, do not touch tip of container to any surface. Replace cap after using
- if solution changes color or becomes cloudy, do not use
- overuse may produce increased redness of the eye
- remove contact lenses before using

Stop use and ask a doctor if

you experience

- eye pain
- changes in vision
- continued redness or irritation of the eye, or if the condition worsens or persists for more than 72 hours

If pregnant or breast-feeding,

ask a health professional before use.

Keep out of reach of children.

If swallowed, get medical help or contact a Poison Control Center (1-800-222-1222) right away.

Directions

Instill 1 or 2 drops in the affected eye(s) up to 4 times daily.

Other information

store at 15º-30ºC (59º-86ºF)

Inactive ingredients

benzalkonium chloride, boric acid, edetate disodium, purified water, sodium chloride, sodium citrate.